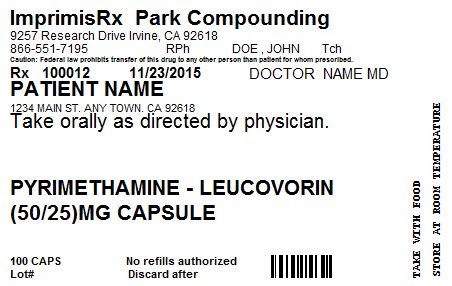 DRUG LABEL: Pyrimethamine Leucovorin
NDC: 70260-480 | Form: CAPSULE
Manufacturer: South Coast Specialty Compounding, Inc. d/b/a Park Compounding
Category: prescription | Type: HUMAN PRESCRIPTION DRUG LABEL
Date: 20151130

ACTIVE INGREDIENTS: PYRIMETHAMINE 50 mg/1 1; LEUCOVORIN CALCIUM 25 mg/1 1
INACTIVE INGREDIENTS: CELLULOSE, MICROCRYSTALLINE 65 mg/1 1

Pyrimethamine Leucovorin (50mg-25mg)